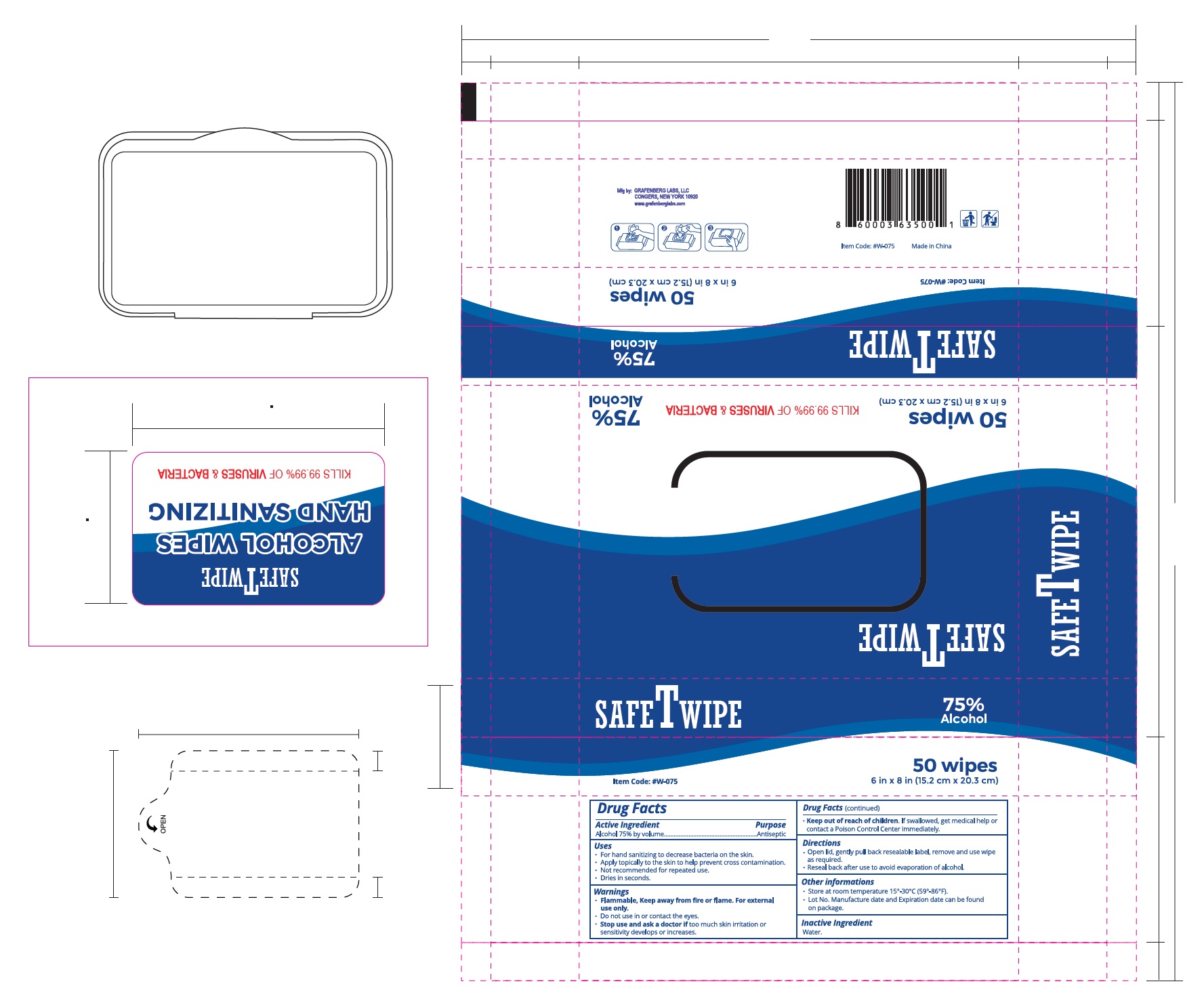 DRUG LABEL: SAFETWIPES
NDC: 77987-001 | Form: CLOTH
Manufacturer: Grafenberg Lab
Category: otc | Type: HUMAN OTC DRUG LABEL
Date: 20200520

ACTIVE INGREDIENTS: ALCOHOL 2.25 mL/1 U
INACTIVE INGREDIENTS: WATER

safeTwipe

The hand sanitizing wipes are manufactured using only the following United States Pharmacopoeia (USP) grade ingredients in the preparation of the product:

Alcohol (75%, v/v).
Hydrogen peroxide (0.125% v/v).
Sterile distilled water or boiled cold water.

The firm does not add other active or inactive ingredients. Different or additional ingredients may impact the quality and potency of the product.

Active Ingredient

Alcohol 75% v/v. Purpose: Antiseptic

Purpose

Antiseptic hand wipes

Use

Hand wipes to help reduce bacteria from skin.

Warning

For external use only. Flammable. Keep away from heat or flame

Do not use in or contact the eyes.

Stop use

Stop use and ask a doctor if irritation or rash occurs.

Keep out

Keep out of reach of children. If swallowed, get medical help or contact a Poison Control Center right away.

Directions

Open label slowly and pull out wipe. Unfold wipe and thoroughly wipe hands. Discard wipe after single use. Make sure to reseal label completely to retain moisture.

Other information

Store at room temperature.

Lot No. Manufacturing date and Expiration date can be found on package.

Inactive ingredient

Water.